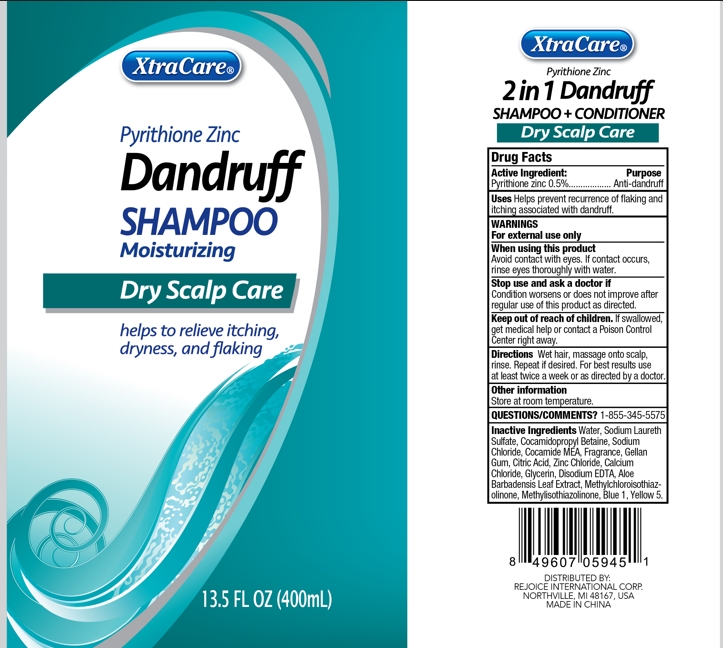 DRUG LABEL: XtraCare Anti-Dandruff Hair Cleanse
NDC: 57337-028 | Form: SHAMPOO
Manufacturer: Rejoice International Inc.
Category: otc | Type: HUMAN OTC DRUG LABEL
Date: 20250409

ACTIVE INGREDIENTS: PYRITHIONE ZINC 20 mg/400 mg
INACTIVE INGREDIENTS: WATER; SODIUM LAURETH SULFATE; COCAMIDOPROPYL BETAINE; SODIUM CHLORIDE; COCO MONOETHANOLAMIDE; .BETA.-D-GLUCOPYRANOSE; GLYCERIN; CARBOMER COPOLYMER TYPE A; DMDM HYDANTOIN; TROLAMINE; EDETATE DISODIUM; FD&C BLUE NO. 1

XTRACARE ANTI-DANDRUFF HAIR CLEANSE FOR SENSITIVE HAIR

Active Ingredient Purpose

Pyrithione zinc 0.5% .................. Anti-dandruff

PURPOSE

XtraCare Anti-Dandruff Shampoo + pyrithione zinc

nourishing coconut & shea butter

fight flakes leaving hair healthy & shiny

Keep out of reach of children. If swallowed, get medical help or contact a Poison Control Center right away.

INDICATIONS AND USAGE

Uses helps prevent recurrence of flaking and itching associated with dandruff.

Gentle enough for everyday use. For best results, use with XtraCare nourishing coconut & shea butter conditioner.

WARNINGS

For external use only

When using this product Avoid contact with eyes. If contact occurs, rinse eyes thoroughly with water.

Stop use and ask a doctor if Condition worsens or does not improve after regular use of this product as directed.

Directions

Wet hair, massage onto scalp, rinse. Repeat if desired. For best results use at least twice a week or as directed by a doctor.

Inactive Ingredients

water, sodium laureth sulfate, cocamidopropyl betaine, sodium chloride, cocamide MEA, lauryl methyl gluceth-10, glycerin, carbomer, DMDM hydantoin, fragrance, triethanolamine, disodium EDTA, cocos nucifera (coconut) fruit extract, shea nut butter.

Other information

store at 20°C to 25°C (68° to 77°F)